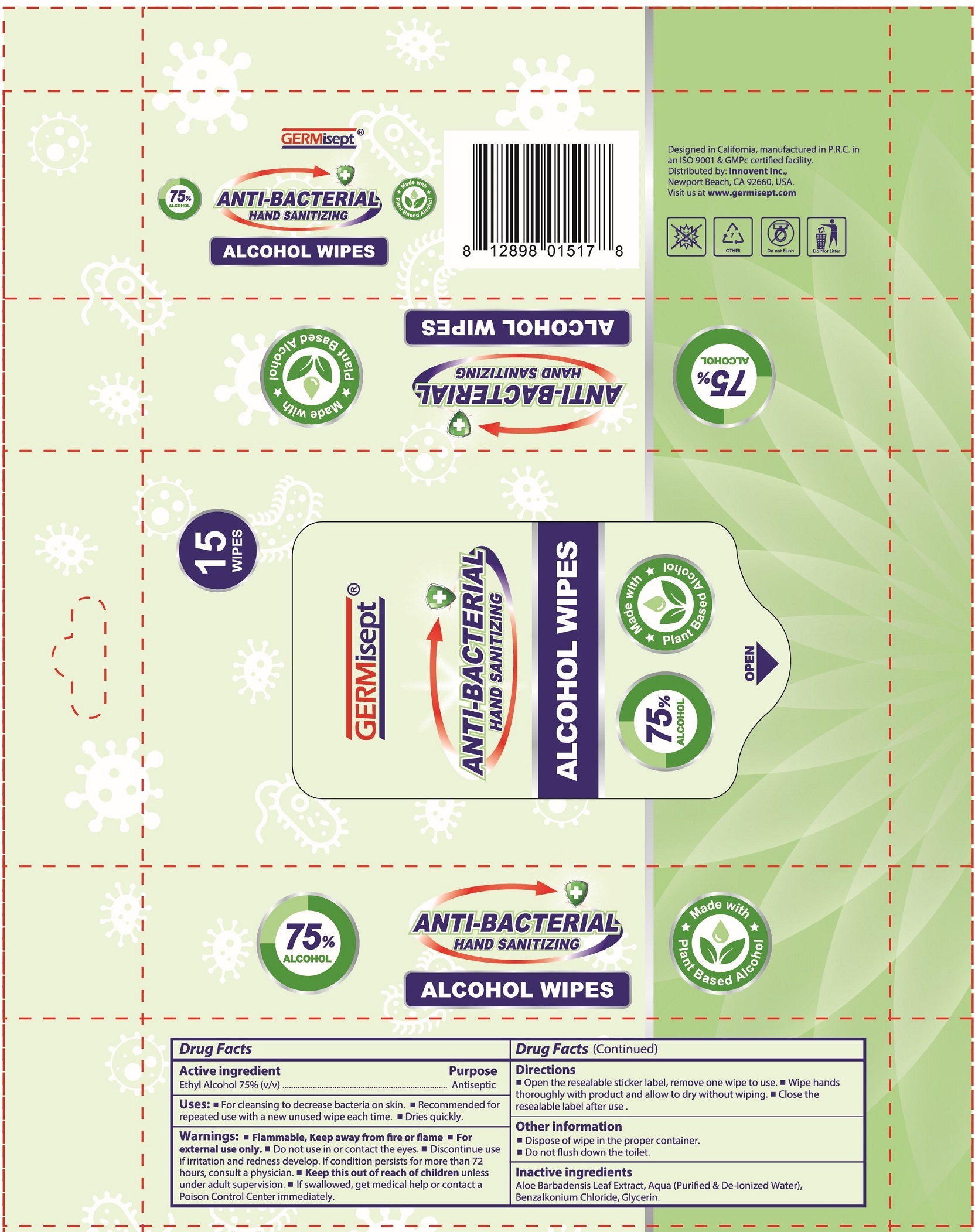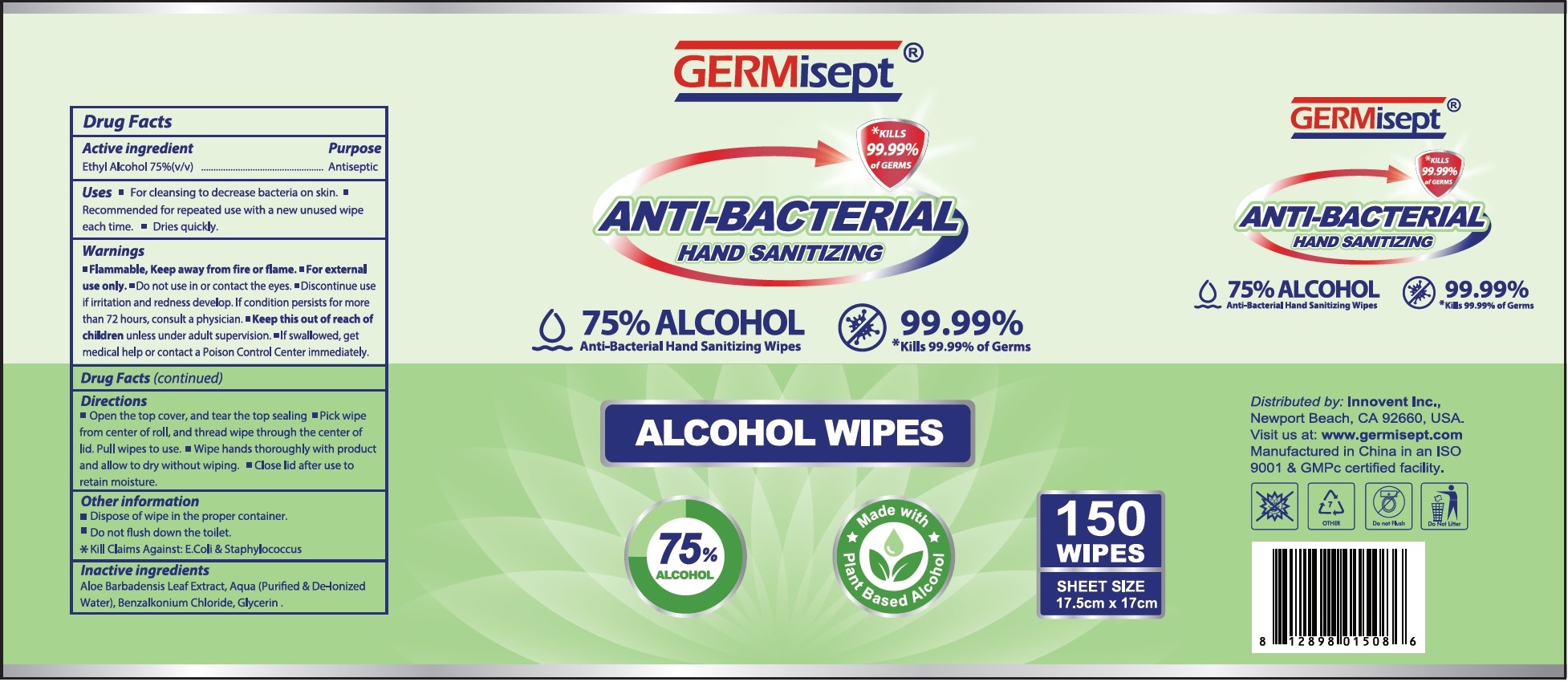 DRUG LABEL: GERMISEPT ANTIBACTERIAL HAND SANITIZING ALCOHOL WIPES
NDC: 70335-010 | Form: CLOTH
Manufacturer: Innovent, Inc.
Category: otc | Type: HUMAN OTC DRUG LABEL
Date: 20231221

ACTIVE INGREDIENTS: ALCOHOL 0.75 mL/1 mL
INACTIVE INGREDIENTS: WATER; ALOE VERA LEAF; BENZALKONIUM CHLORIDE; GLYCERIN

GERMISEPT ANTIBACTERIAL HAND SANITIZING ALCOHOL WIPES

Active ingredient

Ethyl Alcohol 75% (v/v)

Purpose

Antiseptic

Uses:

- For cleansing to decrease bacteria on skin.
- Recommended for repeated use with a new unused wipe each time.
- Dires quickly.

Warnings:

- Flammable, Keep away from fire or flame
- For external use only.

Do not use

- in or contact the eyes.
- Discontinue use if irritation and redness develop. If condition persists for more than 72 hours, consult a physician.

Keep this out of reach of children

- unless under adult supervision.
- If swallowed, get medical help or contact a Poison Control Center immediately.

Directions

- Open the resealable sticker label, remove one wipe to use.
- Wipe hands thoroughly with product and allow to dry without wiping.
- Close the resealable label after use.

Other information

- Dispose of wipe in the proper container.
- Do not flush down the toilet.

Inactive ingredients

Aloe Barbadensis Leaf Extract, Aqua (Purified & De-Ionized Water), Benzalkonium Chloride, Glycerin.